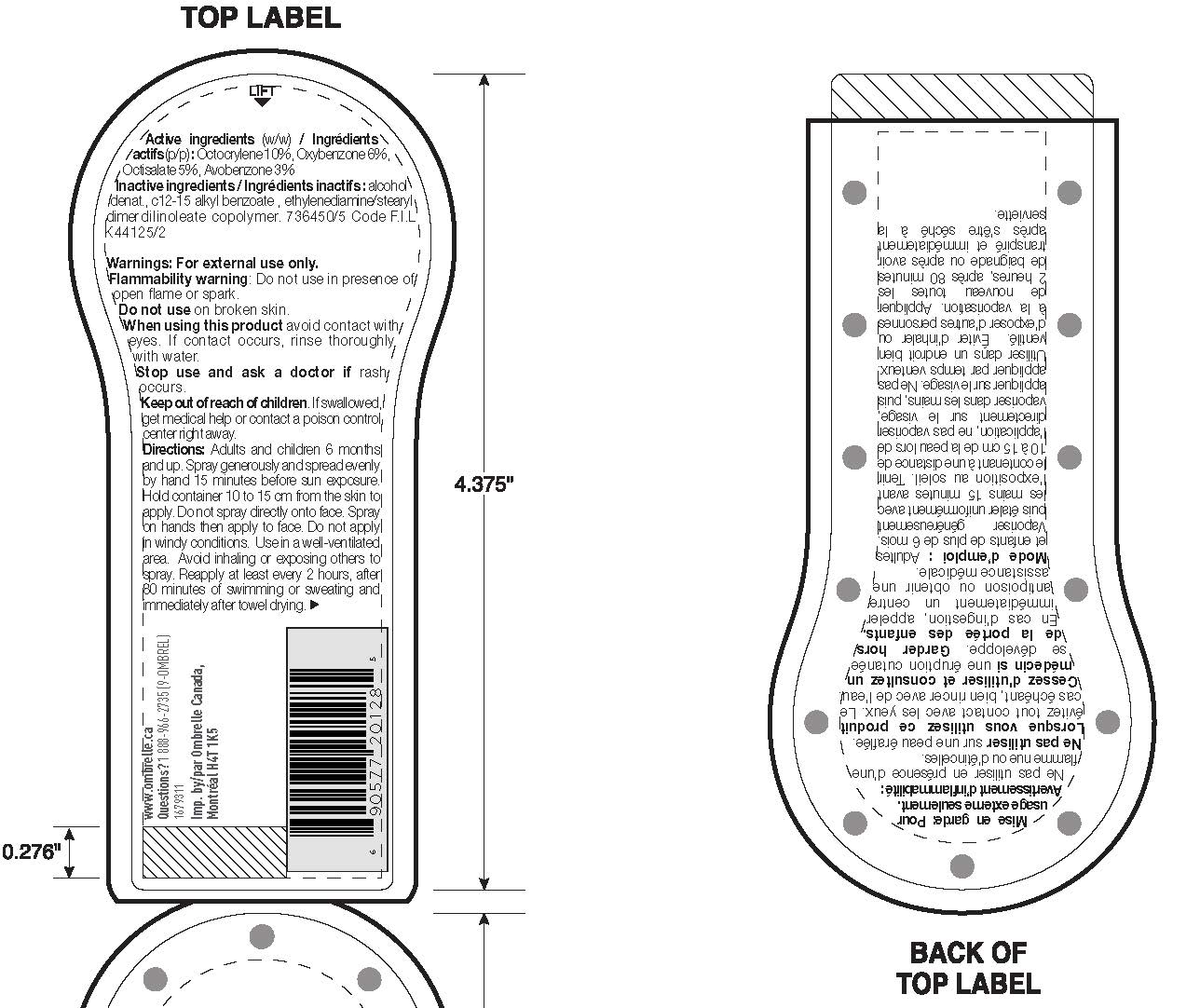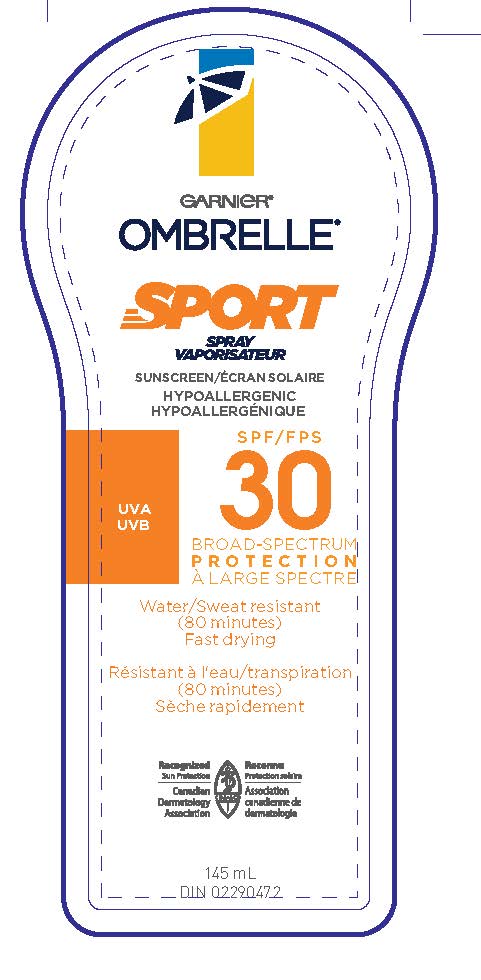 DRUG LABEL: Garnier Ombrelle Sport Vaporisateur Broad Spectrum SPF 30 Sweat Resistant 80 Minutes
NDC: 49967-772 | Form: SPRAY
Manufacturer: L'OREAL USA PRODUCTS INC
Category: otc | Type: HUMAN OTC DRUG LABEL
Date: 20260107

ACTIVE INGREDIENTS: AVOBENZONE 30 mg/1 mL; OCTISALATE 50 mg/1 mL; OCTOCRYLENE 100 mg/1 mL; OXYBENZONE 60 mg/1 mL
INACTIVE INGREDIENTS: ALCOHOL; ALKYL (C12-15) BENZOATE

Drug Facts

Active ingredients

Avobenzone 3%

Octisalate 5%

Octocrylene 10%

Oxybenzone 6%

Warnings

For external use only. Flammability Warning. Do not use in presence of open flame or spark. Do not use on broken skin. When using this product avoid contact with eyes. If contact occurs, rinse thoroughlly with water. Stop use and ask a doctor if rash occurs. Keep out of reach of children. If swallowed get medical help or contact a poison control center right away.

Directions

Adults and children over 6 months and up. Spray generously and spread evenly by hand 15 minutes before sun exposure. Hold container 10 to 15 cm from the skin to apply. Do not spray directly onto face. Spray on hands then apply to face. Do not apply in windy conditions. Use in a well-ventilated area. Reapply at least every 2 hours, after 80 minutes of swimming or sweating, and immediately after towel drying.

Others

alcohol, denat., c12-15 alkyl benzoate, ethylenediamine/stearyl dimer dilinoleate copolymer